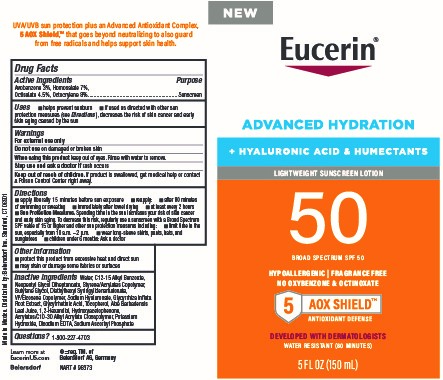 DRUG LABEL: Eucerin Advanced Hydration SPF 50 Sunscreen
NDC: 66800-2000 | Form: LOTION
Manufacturer: Beiersdorf Inc
Category: otc | Type: HUMAN OTC DRUG LABEL
Date: 20251231

ACTIVE INGREDIENTS: OCTOCRYLENE 9 g/100 g; OCTISALATE 4.5 g/100 g; AVOBENZONE 3 g/100 g; HOMOSALATE 9 g/100 g
INACTIVE INGREDIENTS: SODIUM ASCORBYL PHOSPHATE; POTASSIUM HYDROXIDE; NEOPENTYL GLYCOL DIHEPTANOATE; ALOE VERA LEAF; HYDROXYACETOPHENONE; ALKYL (C12-15) BENZOATE; VINYLPYRROLIDONE/EICOSENE COPOLYMER; ENOXOLONE; CARBOMER INTERPOLYMER TYPE A (ALLYL SUCROSE CROSSLINKED); EDETATE DISODIUM; WATER; BUTYLENE GLYCOL; DIETHYLHEXYL SYRINGYLIDENEMALONATE; 1,2-HEXANEDIOL; HYALURONATE SODIUM; GLYCYRRHIZA INFLATA ROOT; STYRENE/ACRYLAMIDE COPOLYMER (MW 500000); TOCOPHEROL

Eucerin Advanced Hydration SPF 50 Sunscreen Lotion

Purpose

Sunscreen

Uses

■ helps prevent sunburn

■ if used as directed with other sun protection measures (see Directions), decreases the risk of skin cancer and early skin aging caused by the sun

Warnings

For external use only

Do not useon damaged or broken skin

WHEN USING

When using this productkeep out of eyes. Rinse with water to remove.

Stop use and ask a doctor ifrash occurs

Keep out of reach of children.If product is swallowed, get medical help or contact a Poison Control Center right away.

Directions

■ apply liberally 15 minutes before sun exposure

■ reapply:

■ after 80 minutes of swimming or sweating

■ immediately after towel drying

■ at least every 2 hours

■ Sun Protection Measures. Spending time in the sun increases your risk of skin cancer and early skin aging. To decrease this risk, regularly use a sunscreen with a Broad Spectrum SPF value of 15 or higher and other sun protection measures including:

■ limit time in the sun, especially from 10 a.m. – 2 p.m.

■ wear long-sleeve shirts, pants, hats, and sunglasses

■ children under 6 months: Ask a doctor

Other information

■ protect this product from excessive heat and direct sun

■ may stain or damage some fabrics or surfaces

Inactive ingredients

Water, C12-15 Alkyl Benzoate, Neopentyl Glycol Diheptanoate, Styrene/Acrylates Copolymer, Butylene Glycol, Diethylhexyl Syringylidenemalonate, VP/Eicosene Copolymer, Sodium Hyaluronate, Glycyrrhiza Inflata Root Extract, Glycyrrhetinic Acid, Tocopherol, Aloe Barbadensis Leaf Juice, 1,2-Hexandiol, Hydroxyacetophenone, Acrylates/C10-30 Alkyl Acrylate Crosspolymer, Potassium Hydroxide, Disodium EDTA, Sodium Ascorbyl Phosphate

Questions?

1-800-227-4703

PACKAGE LABEL

Eucerin®

Advanced Hydration

+Hyaluronic Acid & Humectants

Lightweight Sunscreen Lotion

50 Broad Spectrum SPF 50

Hypoallergenic | Fragrance Free

No Oxybenzone & Octinoxate

5 AOX Shield

Antioxidant Defense

Developed with Dermatologists

Water Resistant (80 Minutes)

5 FL OZ (150 mL)